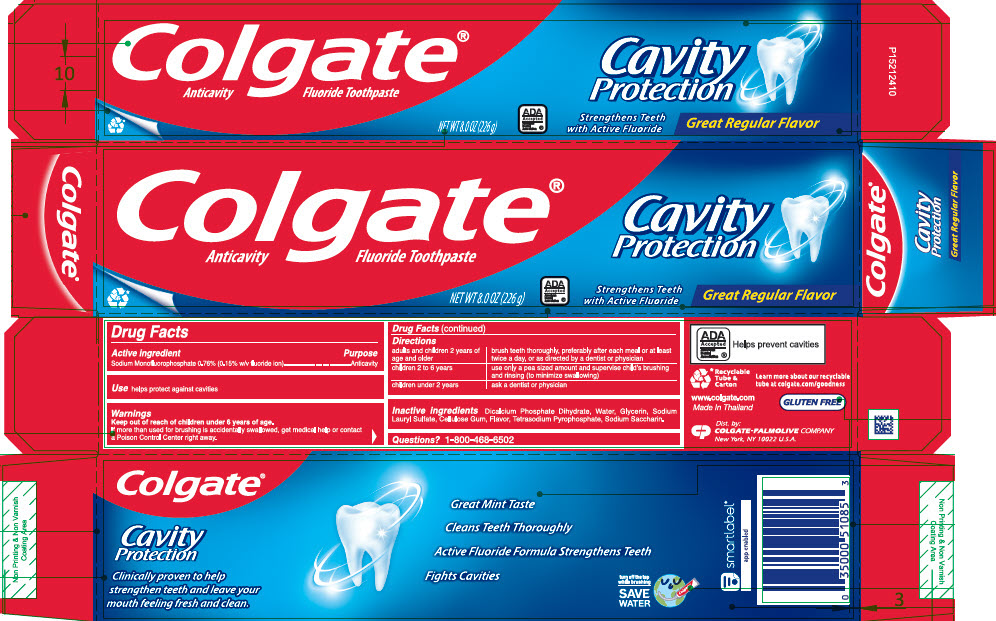 DRUG LABEL: Colgate Cavity Protection Great Regular Flavor
NDC: 35000-060 | Form: PASTE, DENTIFRICE
Manufacturer: Colgate-Palmolive Company
Category: otc | Type: HUMAN OTC DRUG LABEL
Date: 20260122

ACTIVE INGREDIENTS: SODIUM MONOFLUOROPHOSPHATE 1 mg/1 g
INACTIVE INGREDIENTS: DIBASIC CALCIUM PHOSPHATE DIHYDRATE; WATER; GLYCERIN; SODIUM LAURYL SULFATE; CARBOXYMETHYLCELLULOSE SODIUM, UNSPECIFIED; SODIUM PYROPHOSPHATE; SACCHARIN SODIUM

Colgate® Cavity Protection Great Regular Flavor

Drug Facts

Active ingredient

Sodium Monofluorophosphate 0.76% (0.15% w/v fluoride ion)

Purpose

Anticavity

Use

helps protect against cavities

Warnings

Keep out of reach of children under 6 years of age.

If more than used for brushing is accidentally swallowed, get medical help or contact a Poison Control Center right away.

Directions

adults and children 2 years of age and older | brush teeth thoroughly, preferably after each meal or at least twice a day, or as directed by a dentist or physician
children 2 to 6 years | use only a pea sized amount and supervise child's brushing and rinsing (to minimize swallowing)
children under 2 years | ask a dentist or physician

Inactive ingredients

Dicalcium Phosphate Dihydrate, Water, Glycerin, Sodium Lauryl Sulfate, Cellulose Gum, Flavor, Tetrasodium Pyrophosphate, Sodium Saccharin.

Questions?

1-800-468-6502

Dist. by:
COLGATE-PALMOLIVE COMPANY
New York, NY 10022 U.S.A.

PRINCIPAL DISPLAY PANEL - 226 g Tube Carton

Colgate®
Anticavity Fluoride Toothpaste

Cavity
Protection

NET WT 8.0 OZ (226 g)

ADA
Accepted
American
Dental
Association ®

Strengthens Teeth
with Active Fluoride

Great Regular Flavor